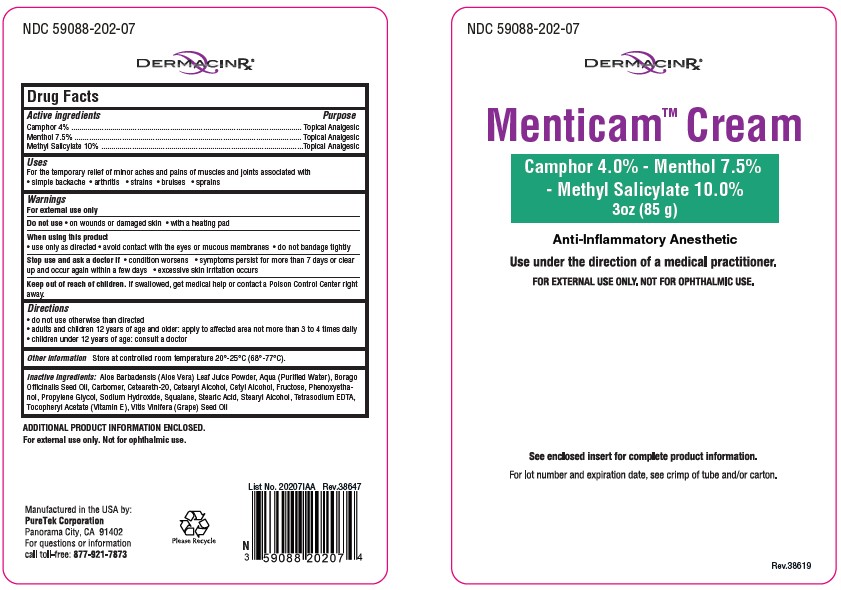 DRUG LABEL: Menticam
NDC: 59088-202 | Form: CREAM
Manufacturer: PureTek Corporation
Category: otc | Type: HUMAN OTC DRUG LABEL
Date: 20241001

ACTIVE INGREDIENTS: CAMPHOR (SYNTHETIC) 4 g/85 g; MENTHOL, UNSPECIFIED FORM 7.5 g/85 g; METHYL SALICYLATE 10 g/85 g
INACTIVE INGREDIENTS: PHENOXYETHANOL; WATER; ALOE VERA LEAF; STEARYL ALCOHOL; .ALPHA.-TOCOPHEROL ACETATE; SODIUM HYDROXIDE; SQUALANE; BORAGE SEED OIL; CETYL ALCOHOL; STEARIC ACID; CARBOMER HOMOPOLYMER, UNSPECIFIED TYPE; CETOSTEARYL ALCOHOL; FRUCTOSE; POLYOXYL 20 CETOSTEARYL ETHER; PROPYLENE GLYCOL; EDETATE SODIUM; GRAPE SEED OIL

Menticam Cream

Active Ingredients

Camphor 4%
Menthol 7.5%
Methyl salicylate 10%

Purpose

Camphor - Topical analgesic
Menthol - Topical analgesic
Methyl Salicylate - Topical analgesic

Uses

For the temporary relief of minor aches and pains of muscles and joints associated with

- simple bachache
- arthritis
- strains
- bruises
- sprains

Warnings

For external use only

Do not use

- on wounds or damaged skin
- with a heating pad
- on a child under 12 years of age with arthritis-like conditions

Ask a doctor before use if you have redness over affected area

When using this product

- avoid contact with the eyes or mucous membranes
- do not bandage tightly

Stop use and ask a doctor if

- condition worsens
- symptoms persist for more than 7 days or clear up and occur again within a few days
- excessive skin irritation occurs

Keep out of reach of children.

If swallowed, get medical help or contact a Poison Control Center right away.

Directions

- do not use otherwise than directed
- adults and children 12 years of age and older: apply to affected area not more than 3 to 4 times daily
- children under 12 years of age: consult a doctor

Other information

Store at controlled room temperature 20°-25°C (68°-77°F)
Avoid excessive heat. Do not use if package is damaged. Keep out of reach of children.

Inactive Ingredients

Aloe Barbadensis (Aloe Vera) Leaf Juice Powder, Aqua (Purified Water), Borago Officinalis Seed Oil, Carbomer, Ceteareth-20, Cetearyl Alcohol, Cetyl Alcohol, Fructose, Phenoxyethanol, Propylene Glycol, Sodium Hydroxide,Squalane, Stearic Acid, Steary Alcohol, Tetrasodium EDTA, Tocopheryl Acetate (Vitamin E), Vitis Vinifera (Grape) Seed Oil

How Supplied

Menticam™ Cream is an anti-inflammatory anesthetic in a 3 oz/ 85 g tube.
NDC 59088-202-07